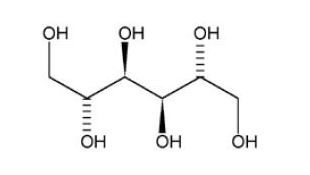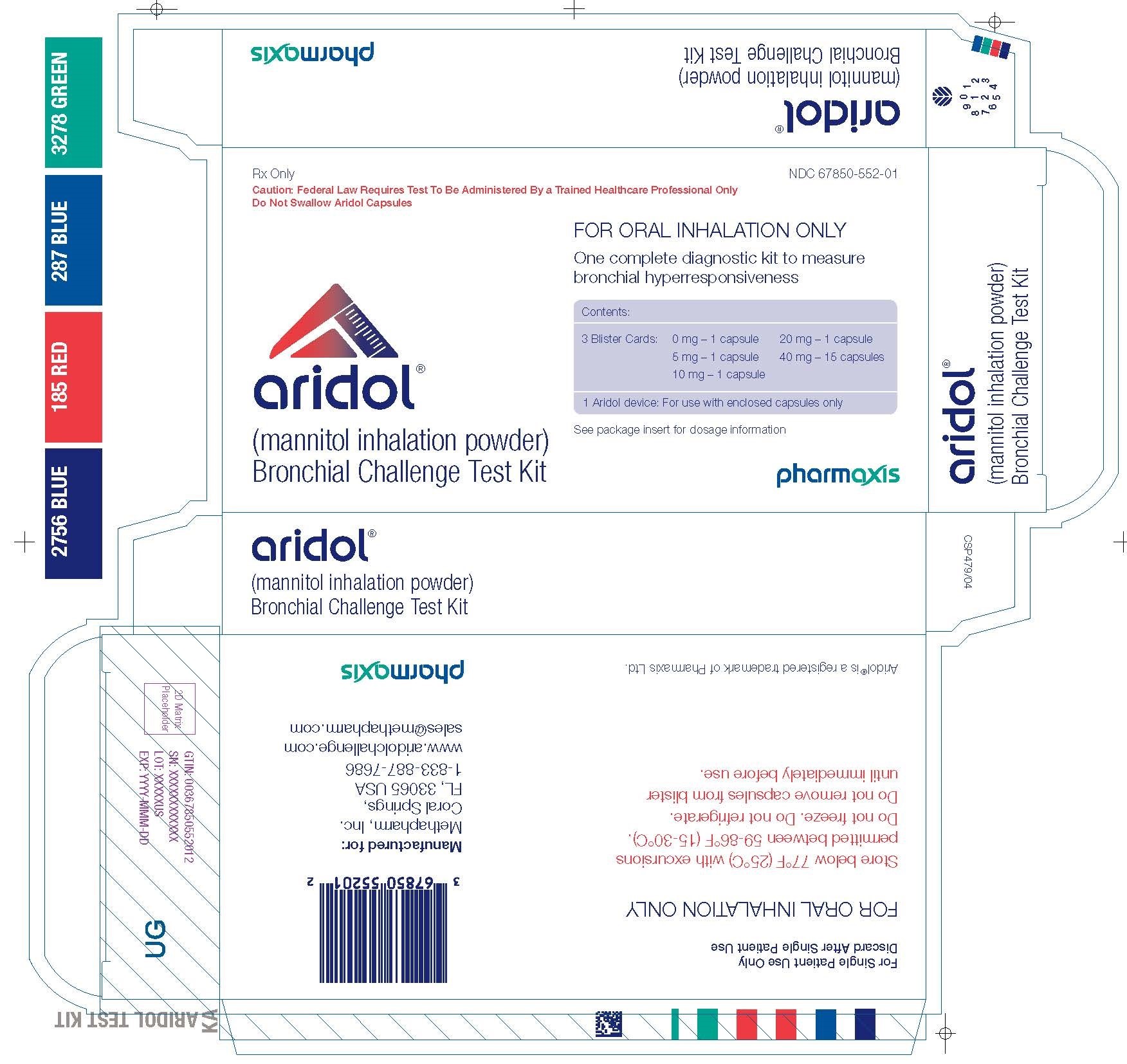 DRUG LABEL: Aridol Bronchial Challenge Test Kit
NDC: 67850-552 | Form: KIT | Route: RESPIRATORY (INHALATION)
Manufacturer: Methapharm, Inc.
Category: prescription | Type: HUMAN PRESCRIPTION DRUG LABEL
Date: 20250213

ACTIVE INGREDIENTS: MANNITOL 5 mg/1 1; MANNITOL 10 mg/1 1; MANNITOL 20 mg/1 1; MANNITOL 40 mg/1 1

HIGHLIGHTS OF PRESCRIBING INFORMATION

These highlights do not include all the information needed to use ARIDOL safely and effectively. See full prescribing information for ARIDOL.
ARIDOL® (mannitol inhalation powder) , for oral inhalation use
Bronchial Challenge Test Kit
Initial U.S. Approval: 1964

WARNING: RISK OF SEVERE BRONCHOSPASM

See full prescribing information for complete boxed warning.

Mannitol, the active ingredient in ARIDOL, acts as a bronchoconstrictor and may cause severe bronchospasm. Bronchial challenge testing with ARIDOL is for diagnostic purposes only. Only trained professionals under the supervision of a physician who are familiar with the management of acute bronchospasm should perform bronchial challenge testing with ARIDOL. Medications (such as short-acting inhaled beta-agonist) and equipment to treat severe bronchospasm must be present in the testing area. Because of the potential for severe bronchoconstriction, bronchial challenge testing with ARIDOL should not be performed in any patient with clinically apparent asthma or very low baseline pulmonary function tests (e.g., FEV1<1-1.5 liters or <70% of the predicted values) (5.1)

1 INDICATIONS AND USAGE

ARIDOL is a sugar alcohol indicated for the assessment of bronchial hyperresponsiveness in adult and pediatric patients 6 years of age or older who do not have clinically apparent asthma. (1)

Limitations of Use: ARIDOL is not a standalone test or a screening test for asthma. Bronchial challenge testing with ARIDOL should be used only as part of a physician's overall assessment of asthma.

2 DOSAGE AND ADMINISTRATION

For Oral Inhalation Use Only

- One ARIDOL test kit contains dry powder mannitol capsules in graduated doses and a single patient use inhaler necessary to perform one bronchial challenge test. (2)
- The mannitol capsules supplied in the ARIDOL kit are to be used with the single patient use inhaler device (2). Discard the inhaler after use.
- Capsule contents are to be inhaled in increasing dosage until either a positive response (15% reduction in FEV1 from baseline or a 10% incremental reduction in FEV1 between consecutive doses) is achieved or all capsules are inhaled (maximum total dose 635mg) (2)
- Starting and maximum dose is the same for children (≥6 years old) and adults (2)

3 DOSAGE FORMS AND STRENGTHS

Inhalation powder: 0mg, 5mg, 10mg, 20mg, and 40mg of mannitol dry powder per capsule in a bronchial challenge test kit (2, 3)

4 CONTRAINDICATIONS

- Known hypersensitivity to mannitol or to the gelatin used to make the capsules (4)
- Conditions that may be compromised by induced bronchospasm or repeated spirometry maneuvers (4)

5 WARNINGS & PRECAUTIONS

- Severe bronchospasm: ARIDOL may cause severe bronchospasm in susceptible patients. Administer by trained professionals under the supervision of a physician. Medications and equipment to treat severe bronchospasm must be present in the testing area. (5.1)
- Subjects with co-morbid conditions: Use with caution in patients with conditions that may increase sensitivity to the bronchoconstricting or other potential effects of ARIDOL such as: severe cough, ventilatory impairment, unstable angina, or active upper or lower respiratory tract infection that may worsen with use of a bronchial irritant. (5.2)

6 ADVERSE REACTIONS

Most common adverse reactions (rate ≥1%) were headache, pharyngolaryngeal pain, throat irritation, nausea, cough, rhinorrhea, dyspnea, chest discomfort, wheezing, retching and dizziness. (6.1)

To report SUSPECTED ADVERSE REACTIONS, contact Methapharm, Inc. at 1-866-701-4636 or email at medinfo@methapharm.com or FDA at 1-800-FDA-1088 or www.fda.gov/medwatch

FULL PRESCRIBING INFORMATION

WARNING: RISK OF SEVERE BRONCHOSPASM

Mannitol, the active ingredient in ARIDOL, acts as a bronchoconstrictor and may cause severe bronchospasm. Bronchial challenge testing with ARIDOL is for diagnostic purposes only. Bronchial challenge testing with ARIDOL should only be conducted by trained professionals under the supervision of a physician familiar with all aspects of the bronchial challenge test and the management of acute bronchospasm. Medications (such as short-acting inhaled beta-agonist) and equipment to treat severe bronchospasm must be present in the testing area. If severe bronchospasm occurs it should be treated immediately by administration of a short-acting inhaled beta-agonist. Because of the potential for severe bronchoconstriction, the bronchial challenge testing with ARIDOL should not be performed in any patient with clinically apparent asthma or very low baseline pulmonary function tests (e.g., FEV1 <1-1.5 liters or <70% of the predicted values) [see Warnings and Precautions (5.1)].

1 INDICATIONS AND USAGE

ARIDOL is indicated for the assessment of bronchial hyperresponsiveness in adult and pediatric patients 6 years of age or older who do not have clinically apparent asthma.

Limitations of Use:
ARIDOL is not a standalone test or a screening test for asthma. Bronchial challenge testing with ARIDOL should be used only as part of a physician's overall assessment of asthma.

2 DOSAGE AND ADMINISTRATION

2.1 Bronchial Challenge Test Kit Overview

ARIDOL is a bronchial challenge test kit containing the required capsules of dry powder mannitol for oral inhalation in graduated doses with the supplied single patient use inhaler necessary to perform one bronchial challenge test. Do not swallow ARIDOL capsules.

The airway response to bronchial challenge testing with ARIDOL is measured using forced expiratory volume in one second (FEV1).

Prior to bronchial challenge testing with ARIDOL, standard spirometry should be performed and the reproducibility of the resting FEV1 established.

2.2 Administration Instructions

An overview of the testing procedure can be found below. The ARIDOL bronchial challenge test should only be used with the provided inhaler. All remaining unused (opened and unopened) blister packs and the inhaler should be properly discarded at the completion of the test. See the ARIDOL Bronchial Challenge Test Kit instructions for complete instructions on the dosing and spirometry procedures.

a. A nose clip may be used if preferred. If so, apply nose clip to the patient and direct the patient to breathe through the mouth

b. Insert 0 mg capsule into inhalation device. Puncture capsule by depressing buttons on side of device slowly, and ONCE ONLY (a second puncture may fragment the capsules)

c. The patient should exhale completely, before inhaling from device in a controlled deep inspiration

d. At the end of deep inspiration, start 60 second timer, subject should hold breath for 5 seconds and exhale through mouth before removal of nose clip

e. At the end of 60 seconds, measure the FEV1 in duplicate (the measurement after inhaling the 0 mg capsule is the baseline FEV1)

f. Repeat steps a-e following the mannitol capsule dose steps from Table 1 below until the patient has a positive response or 635 mg of mannitol has been administered (negative test)

Table 1: Mannitol dose steps for bronchial challenge testing with ARIDOL
Dose # | Dose mg | Cumulative Dose mg | Capsules per dose
1 | 0 | 0 | 1
2 | 5 | 5 | 1
3 | 10 | 15 | 1
4 | 20 | 35 | 1
5 | 40 | 75 | 1
6 | 80 | 155 | 2 x 40 mg
7 | 160 | 315 | 4 x 40 mg
8 | 160 | 475 | 4 x 40 mg
9 | 160 | 635 | 4 x 40 mg

2.3 Bronchial Challenge Test Response and Patient Management

A positive response is achieved when the patient experiences a 15% reduction in FEV1 from (0 mg) baseline (or a 10% incremental reduction in FEV1 between consecutive doses). The test result is expressed as a PD15.

Patients with either a positive response to bronchial challenge testing with ARIDOL or significant respiratory symptoms should receive a standard dose of a short-acting inhaled beta-agonist and monitored until fully recovered to within baseline.

3 DOSAGE FORMS AND STRENGTHS

Inhalation powder: 0 mg, 5 mg, 10 mg, 20 mg, and 40 mg of mannitol dry powder per capsule in a bronchial challenge test kit.

Each kit contains one, single patient use, dry powder inhaler device and 3 consecutively numbered foil blister packs containing a total of 19 capsules of mannitol for oral inhalation as described below:

Blister pack "1":

- Marked 1 - 1 x empty clear capsule printed with two white bands
- Marked 2 - 1 x 5 mg white/clear capsule printed with 5 mg
- Marked 3 - 1 x 10 mg yellow/clear capsule printed with 10 mg
- Marked 4 - 1 x 20 mg pink/clear capsule printed with 20 mg

Blister pack "2":

- Marked 5 - 1 x 40 mg red/clear capsule printed with 40 mg
- Marked 6 - 2 x 40 mg red/clear capsules printed with 40 mg
- Marked 7 - 4 x 40 mg red/clear capsules printed with 40 mg

Blister pack "3":

- Marked 8 - 4 x 40 mg red/clear capsules printed with 40 mg
- Marked 9 - 4 x 40 mg red/clear capsules printed with 40 mg

4 CONTRAINDICATIONS

ARIDOL is contraindicated in:

- Patients with known hypersensitivity to mannitol or to the gelatin used to make the capsules
- Patients with conditions that may be compromised by induced bronchospasm or repeated spirometry maneuvers. Some examples include: aortic or cerebral aneurysm, uncontrolled hypertension, recent myocardial infarction or cerebral vascular accident [see Warnings and Precautions (5.2)].

5 WARNINGS & PRECAUTIONS

5.1 Severe Bronchospasm

Mannitol, the active ingredient in ARIDOL, acts as a bronchoconstrictor and may cause severe bronchospasm in susceptible patients. The test should only be conducted by trained professionals under the supervision of a physician familiar with all aspects of the bronchial challenge test and the management of acute bronchospasm. Patients should not be left unattended during the bronchial challenge test. Medications and equipment to treat severe bronchospasm must be present in the testing area.

If a patient has a ≥10% reduction in FEV1 (from pre-challenge FEV1) on administration of the 0 mg capsule, the ARIDOL Bronchial Challenge Test should be discontinued and the patient should be given a dose of a short-acting inhaled beta-agonist and monitored accordingly.

Patients with either a positive response to bronchial challenge testing with ARIDOL or significant respiratory symptoms should receive a short-acting inhaled beta-agonist. Patients should be monitored until fully recovered to within baseline.

5.2 Subjects with Co-morbid Conditions

Bronchial challenge testing with ARIDOL should be performed with caution in patients with conditions that may increase sensitivity to the bronchoconstricting or other potential effects of ARIDOL such as severe cough, ventilatory impairment, spirometry-induced bronchoconstriction, hemoptysis of unknown origin, pneumothorax, recent abdominal or thoracic surgery, recent intraocular surgery, unstable angina, or active upper or lower respiratory tract infection.

6 ADVERSE REACTIONS

The following clinically significant adverse reaction is described elsewhere in the labeling:
• Severe Bronchospasm [see Warnings and Precautions (5.1)].

6.1 Clinical Trials Experience

Because clinical trials are conducted under widely varying conditions, adverse reaction rates observed in the clinical trials of a drug cannot be directly compared to rates in the clinical trials of another drug and may not reflect the rates observed in practice.

The safety population for the ARIDOL bronchial challenge test consisted of 1,082 subjects (577 females and 505 males) including patients with asthma, symptoms suggestive of asthma, and healthy individuals from 6 to 83 years of age who participated in the two clinical trials (Studies 1 and 2). The racial distribution of subjects was 84% Caucasian, 5% Asian, 4% Black, and 7% Other. Pediatric and adolescents patients comprised 23% of the total study population with 118 pediatric patients aged 6-11 years and 128 adolescents aged 12-17 years.

Adverse reactions were reported at the time of the testing procedure and for one day thereafter. No serious adverse reactions were reported following bronchial challenge testing with ARIDOL in either trial.

Five adult subjects (0.6%) discontinued from the studies within a day following bronchial challenge testing with ARIDOL because of cough, decreased lung function, feeling jittery, sore throat, and throat irritation. One adult subject (0.3%) discontinued following the methacholine bronchial challenge test because of dizziness. One pediatric subject (0.4%) discontinued from the studies within a day following bronchial challenge testing with ARIDOL because of retching.

Table 2 displays the combined common adverse reactions (≥1%) within a day after bronchial challenge testing with ARIDOL or methacholine in the overall population for Studies 1 and 2.

Table 2: Adverse reactions with an incidence ≥1% within a day after bronchial challenge testing (overall population, Studies 1 and 2 combined)
Adverse Reactions | Treatment
Adverse Reactions | ARIDOL (N=1046) n (%) | Methacholine Challenge (N=420) n (%)
Headache | 59 (6) | 4 (1)
Pharyngolaryngeal pain | 25 (2) | 0
Throat irritation | 19 (2) | 1 (<1)
Nausea | 19 (2) | 0
Cough | 17 (2) | 8 (2)
Rhinorrhea | 16 (2) | 0
Dyspnea | 15 (1) | 21 (5)
Chest discomfort | 13 (1) | 18 (4)
Wheezing | 8 (1) | 6 (1)
Retching | 6 (1) | 0
Dizziness | 5 (1) | 13 (3)

The maximum reduction in FEV1 following bronchial challenge testing with ARIDOL was 46%, compared to 54% for exercise testing and 67% for the methacholine challenge. The incidences in decreases in FEV1 ≥30% and ≥60% following ARIDOL, methacholine, and exercise challenges for Studies 1 and 2 is shown in Table 3.

Table 3: Incidence of decreases in FEV1 ≥30% or ≥60% (overall population, Studies 1 and 2)
Challenge | No. Exposed | N (%) with Fall in FEV1 ≥30% | N (%) with Fall in FEV1 ≥60%
Study 1
Exercise | 435 | 27 (6%) | 0
Methacholine | 420 | 51 (12%) | 3 (1%)
ARIDOL | 419 | 3 (1%) | 0
Study 2
ARIDOL asthmatics | 536 | 23 (4%) | 0
ARIDOL Non-asthmatics | 91 | 0 | 0

There were no differences in the incidence of adverse reactions based on gender or race. The clinical trials did not include sufficient numbers of subjects 65 years of age and older to determine whether they respond differently compared to subjects below 65 years of age.

Pediatric Patients Aged 6 to 17 Years: Overall, the types and severities of adverse reactions in children were similar to those observed in the adult population. As in the adult population, the adverse reactions of pharyngolaryngeal pain, nausea, and headache were the more common with incidences of 4%, 3%, and 3%, respectively. There were no major differences in the types of adverse reactions observed in children 6-11 years of age compared to adolescents 12-17 years old.

The decrease in FEV1 in pediatric patients and adolescents who received the ARIDOL bronchial challenge test was similar to that of the adult population with 5%, 15% and 9% of pediatric patients who had bronchial challenge testing with ARIDOL, methacholine and exercise, respectively, experiencing reduction in FEV1 ≥30%. No patient who had bronchial challenge testing with ARIDOL or exercise had a decrease in FEV1 ≥60%, whereas, one adolescent patient (aged 12 years) who received methacholine had a decrease in FEV1 ≥60%.

6.2 Post-Marketing Experience

The following adverse reactions have been identified post approval outside the U.S. of the ARIDOL Bronchial Challenge Test Kit: cough, gagging, wheeze, and decreased forced expiratory volume. Because these reactions are reported voluntarily from a population of uncertain size, it is not always possible to reliably estimate their frequency or establish a causal relationship to drug exposure.

7 DRUG INTERACTIONS

No formal drug-drug interaction studies were conducted with mannitol, the active ingredient in ARIDOL.

8 USE IN SPECIFIC POPULATIONS

8.1 Pregnancy

Risk Summary

There are no available human data regarding inhaled mannitol to evaluate a drug-associated risk for major birth defects, miscarriage, or other adverse maternal or fetal outcomes. Based on animal reproduction studies, no evidence of structural alterations was observed when mannitol was orally administered to pregnant rats and mice during organogenesis at doses up to approximately 20 and 10 times, respectively, the maximum recommended daily inhalation dose (MRDID) in humans (see Data).

The estimated background risk of major birth defects and miscarriage for the indicated population is unknown. All pregnancies have a background risk of birth defect, loss, or other adverse outcomes. In the United States general population, the estimated background risk of major birth defects and miscarriage in clinically recognized pregnancies is 2-4% and 15-20%, respectively

Data

Animal Data

In animal reproduction studies, oral administration of mannitol to pregnant rats and mice during the period of organogenesis did not cause fetal structural alterations. The mannitol dose in rats and mice was approximately 20 and 10 times the maximum recommended human daily inhalation dose (MRDID) in humans, respectively, (on a mg/m2 basis at maternal doses of 1600 mg/kg/day in both
species).

8.2 Lactation

Risk Summary

There are no data on the presence of mannitol in human or animal milk, the effects on the breastfed infant, or the effects on milk production. The developmental and health benefits of breastfeeding should be considered along with the mother’s clinical need for ARIDOL bronchial challenge test and any potential adverse effects on the breastfed child from ARIDOL or from the underlying maternal condition.

8.4 Pediatric Use

The safety and effectiveness of ARIDOL for the assessment of bronchial hyperresponsiveness in adult and pediatric patients 6 years of age or older who do not have clinically apparent asthma have been established. The use of ARIDOL for this indication is supported by evidence from two clinical studies that included 246 pediatric patients 6 to 17 years of age [see Clinical Studies (14)].

The mean and median maximum percentage reduction in FEV1 in patients with a positive ARIDOL challenge test in pediatric patients 6 to 17 years of age (19% and 18%, respectively) showed no apparent difference compared to the adult population (19% and 18%, respectively).

The safety profile of the ARIDOL bronchial challenge test in pediatric patients 6 to 17 years of age was similar to the adult population in two clinical studies [see Adverse Reactions (6)].

Safety and effectiveness of ARIDOL have not been established in pediatric patients less than 6 years old. Bronchial challenge testing with ARIDOL should not be performed in children less than 6 years of age due to their inability to provide reliable spirometric measurements.

8.5 Geriatric Use

Clinical studies of ARIDOL did not include sufficient numbers of patients 50 years of age and older to determine whether they respond differently from younger adult patients.

8.6 Hepatic and Renal Impairment

Formal pharmacokinetic studies with mannitol, the active ingredient, in ARIDOL, have not been conducted in patients with hepatic or renal impairment. However, an increase in systemic exposure of mannitol can be expected in patients with renal impairment based on the kidney being its primary route of elimination.

Given parenterally, mannitol is used as an osmotic diuretic in a variety of clinical situations including acute renal failure where the osmotic effects of mannitol inhibit the rate of water re-absorption and maintain the rate of urine production.

10 OVERDOSAGE

Susceptible persons may experience excessive bronchospasm from an overdosage. If such bronchospasm occurs, immediately administer a short-acting inhaled beta-agonist and other medical treatments such as oxygen, as necessary.

11 DESCRIPTION

D-mannitol (referred to throughout as mannitol), the active ingredient in ARIDOL is a hexahydric alcohol, that is a sugar alcohol, with the following chemical name (2R,3R,4R,5R)-hexane-1,2,3,4,5,6-hexol and chemical structure:

Mannitol is a white or almost white crystalline powder of free-flowing granules with an empirical formula of C6H14O6 and molecular weight of 182.2. Mannitol is freely soluble in water, and very slightly soluble in alcohol. Mannitol shows polymorphism.

The ARIDOL Bronchial Challenge Test Kit contains one single patient use dry powder inhaler and 3 consecutively numbered foil blister packs containing a total of 19 capsules of mannitol for oral inhalation. All except the 0 mg printed hard gelatin capsules contain dry powder mannitol for oral inhalation. The accompanying dry powder inhaler is a plastic device used for inhaling the capsules. All doses are to be administered using the same device supplied with each kit without washing or sterilizing the device at anytime during the test.

To use the delivery system, a mannitol capsule is placed in the well of the inhaler, and the capsule is pierced by pressing and releasing the buttons ONCE on the side of the device. The mannitol dry powder is dispersed into the air stream when the patient inhales deeply through the mouthpiece.

There are no inactive ingredients in the mannitol capsules supplied with the ARIDOL Bronchial Challenge Test Kit. The 0 mg capsule and the bodies of the 5, 10, 20 and 40 mg capsules are clear. The white caps (5 mg) contain titanium dioxide. The yellow caps (10 mg) contain titanium dioxide and yellow iron oxide. The pink caps (20 mg) and red caps (40 mg) contain titanium dioxide and red iron dioxide. The inhaler is a plastic device used for administering mannitol to the lungs. The amount of drug delivered to the lung will depend on patient factors, such as inspiratory flow rate and inspiratory time. Under standardized in vitro testing at a fixed flow rate of 60 L/min for 2 seconds, the delivered dose from the inhaler from each of the 5, 10, 20 and 40 mg capsules is approximately 3.4, 7.7, 16.5 and 34.1 mg, respectively. Peak inspiratory flow rates (PIFR) achievable through the inhaler were evaluated in healthy and asthmatic individuals ranging from 7 to 65 years of age and with % FEV1 of predicted ranging from 67% to 123%. PIFR achieved in the study was at least 70.8 L/min in all subjects assessed. The mean PIFR was 118.2 L/min and approximately ninety percent of each population studied generated a PIFR through the device exceeding 90 L/min.

12 CLINICAL PHARMACOLOGY

12.1 Mechanism of Action

The precise mechanisms through which inhaled mannitol causes bronchoconstriction are not known.

12.2 Pharmacodynamics

The response to inhaled mannitol is reported as the delivered dose of mannitol causing a 15% reduction in FEV1 and is expressed as PD15.

12.3 Pharmacokinetics

Absorption: The rate and extent of absorption of mannitol after oral inhalation was generally similar to that observed after oral administration. In a study of 18 healthy adult male subjects the absolute bioavailability of mannitol powder following oral inhalation was 59% while the relative bioavailability of inhaled mannitol in comparison to orally administered mannitol was 96%. Following oral inhalation of 635 mg, the mean mannitol peak plasma concentration (Cmax) was 13.71 mcg/mL while the mean extent of systemic exposure (AUC) was 73.15 mcg•hr/mL. The mean time to peak plasma concentration (Tmax) after oral inhalation was 1.5 hour.

Distribution: Based on intravenous administration, the volume of distribution of mannitol was 34.3 L.

Elimination: Following oral inhalation, the elimination half-life of mannitol was 4.7 hours. The mean terminal elimination half-life for mannitol in plasma remained unchanged regardless of the route of administration (oral, inhalation, and intravenous). The urinary excretion rate versus time profile for mannitol was consistent for all routes of administration. The total clearance after intravenous administration was 5.1 L/hr while the renal clearance was 4.4 L/hr. Therefore, the clearance of mannitol was predominately via the kidney. Following inhalation of 635 mg of mannitol in 18 healthy subjects, about 55% of the total dose was excreted in the urine as unchanged mannitol. Following oral or intravenous administration of a 500 mg dose, the corresponding values were 54% and 87% of the dose, respectively.

Metabolism: The extent of metabolism of mannitol appears to be small. This is evident from a urinary excretion of about 87% of unchanged drug after an intravenous dose to healthy subjects.

Specific Populations

Patients with Hepatic and Renal Impairment: Formal pharmacokinetic studies using ARIDOL have not been conducted in patients with hepatic or renal impairment. Since the drug is eliminated primarily via the kidney, an increase in systemic exposure can be expected in renally impaired patients.

13 NONCLINICAL TOXICOLOGY

13.1 Carcinogenesis, Mutagenesis, Impairment of Fertility

In 2-year carcinogenicity studies in rats and mice, mannitol did not show evidence of carcinogenicity at oral dietary concentrations up to 5% (or 7,500 mg/kg on a mg/kg basis). These doses were approximately 55 and 30 times the MRHDID, respectively, on a mg/m^2 basis.

Mannitol tested negative in the following assays: bacterial gene mutation assay, in vitro mouse lymphoma assay, in vitro chromosomal aberration assay in WI-38 human cells, in vivo chromosomal aberration assay in rat bone marrow, in vivo dominant lethal assay in rats, and in vivo mouse micronucleus assay.

The effect of inhaled mannitol on fertility has not been investigated.

14 CLINICAL STUDIES

The effectiveness of the ARIDOL Bronchial Challenge Test Kit in assessing bronchial hyperresponsiveness in adults and children 6 years of age and older was assessed in two clinical studies. Study 1 was an operator-blinded, open-label crossover trial that assessed the sensitivity and specificity of bronchial challenge testing with ARIDOL compared with a methacholine bronchial challenge test in detecting bronchial hyperresponsiveness in subjects with symptoms suggestive of asthma but without a definite diagnosis of asthma. During the course of the study subjects underwent three types of bronchial challenge tests utilizing exercise, ARIDOL, and methacholine. A positive exercise test was defined as a decrease in FEV1 ≥10%, a positive bronchial challenge test with ARIDOL was defined by either a decrease in FEV1 by ≥15% from baseline or a between-dose reduction in FEV1 ≥10%, and a positive methacholine response was defined as a decrease in FEV1 ≥20% after breathing methacholine at a concentration less than or equal to 16 mg/mL. The sensitivity and specificity of bronchial challenge testing with ARIDOL and methacholine were then assessed relative to exercise testing which served as a common comparator. The sensitivity and specificity of ARIDOL and methacholine challenges were also assessed using a blinded study physician's diagnosis of asthma at the end of the study. Five-hundred nine subjects aged 6 to 50 years were screened for enrolment with 419 and 420 subjects receiving at least one dose of mannitol, the active ingredient in ARIDOL, or methacholine, respectively. The maximum cumulative dose of mannitol was 635 mg. Bronchial challenge testing with ARIDOL and methacholine demonstrated similar sensitivity and specificity in predicting bronchial hyperresponsiveness defined by a positive exercise challenge (Table 4).

Table 4: Comparisons of the sensitivity and specificity (calculated relative to exercise challenge) for the ARIDOL test and methacholine in Study 1
Population | Treatment | Sensitivity % (95% CI) | Specificity % (95% CI)
Overall Population (n=419)
 | ARIDOL | 58 (50, 65) | 63 (57, 69)
 | Methacholine | 53 (46, 51) | 68 (62, 73)
 | Difference | 5 (-4, 13) | -5 (-12, 3)
Age 6-11 years old (n=36)
 | ARIDOL | 67 (47, 87) | 47 (21, 72)
 | Methacholine | 71 (52, 91) | 33 (9, 57)
 | Difference | -5 (-29, 20) | 17 (-29, 62)
Age 12-17 years old (n=70)
 | ARIDOL | 55 (37, 72) | 62 (46, 77)
 | Methacholine | 65 (48, 81) | 64 (49, 79)
 | Difference | -10 (32, 13) | -3 (-24, 19)

Bronchial challenge testing with ARIDOL and methacholine also demonstrated similar sensitivity and specificity when calculated relative to a blinded study physician's diagnosis of asthma in subjects at the end of the study.

The sensitivity and specificity of bronchial challenge testing with ARIDOL in children and adolescents 6 to 17 years of age in Study 1 was similar to that in the overall population (Table 4).

Study 2 was a crossover study comparing bronchial challenge testing with ARIDOL to hypertonic (4.5%) saline in identifying bronchial hyperresponsiveness in subjects 6 to 83 years of age with (n=551) and without (n=95) asthma. In this study the efficacy endpoint of interest was an estimation of the sensitivity and specificity of bronchial challenge testing with ARIDOL with respect to a physician's clinical diagnosis of asthma. Following completion of the bronchial challenge tests with ARIDOL and hypertonic saline, a respiratory physician assessed the data and categorized the subjects as having or not having asthma. The sensitivity of the ARIDOL bronchial challenge test in subjects with a physician diagnosis of asthma was 58% [(54%, 62%, 95th CI)] compared to a sensitivity of the physician diagnosis in the same population of 97% [(95%, 98%, 95th CI)]. The specificity of the ARIDOL bronchial challenge test in subjects without asthma was 95% [(90%, 99%, 95th CI)] compared to the specificity of the physician diagnosis of 98% [(95%, 100%, 95th CI)].

16 HOW SUPPLIED/STORAGE AND HANDLING

How Supplied

ARIDOL is a bronchial challenge test kit. Each kit contains one single patient use, dry powder inhaler device and 3 consecutively numbered foil blister packs containing a total of 19 capsules of dry powder mannitol for oral inhalation as described below:

Blister pack "1":

- Marked 1 - 1 x empty clear capsule printed with two white bands
- Marked 2 - 1 x 5 mg white/clear capsule printed with 5 mg
- Marked 3 - 1 x 10 mg yellow/clear capsule printed with 10 mg
- Marked 4 - 1 x 20 mg pink/clear capsule printed with 20 mg

Blister pack "2":

- Marked 5 - 1 x 40 mg red/clear capsule printed with 40 mg
- Marked 6 - 2 x 40 mg red/clear capsules printed with 40 mg
- Marked 7 - 4 x 40 mg red/clear capsules printed with 40 mg

Blister pack "3":

- Marked 8 - 4 x 40 mg red/clear capsules printed with 40 mg
- Marked 9 - 4 x 40 mg red/clear capsules printed with 40 mg

NDC-67850-552-01

Storage

Store below 77°F (25°C) with excursions permitted between 59°F-86°F (15°C-30°C). [See USP Controlled Room Temperature]. Do not freeze. Do not refrigerate.

17 PATIENT COUNSELING INFORMATION

Severe Bronchospasm

Prior to administration patients should be informed of the potential for bronchial challenge testing with ARIDOL to cause severe bronchospasm and of the potential symptoms they may experience [see Warnings and Precautions (5.1)].

Patients with Certain Co-morbid Conditions

Bronchial challenge testing with ARIDOL should be performed with caution in patients having severe cough, ventilatory impairment, spirometry-induced bronchoconstriction, hemoptysis of unknown origin, pneumothorax, recent abdominal or thoracic surgery, recent intraocular surgery, unstable angina, or active upper or lower respiratory tract infection or other conditions that may worsen with the use of a bronchial irritant [see Warnings and Precautions (5.2)].

Manufactured by:

Arna Pharma Pty Ltd

20 Rodborough Rd

Frenchs Forest NSW 2086

AUSTRALIA

Manufactured for:

Methapharm, Inc.

11772 West Sample Road, Suite 101 Coral Springs,

FL, 33065 USA

1-833-887-7686 www.aridolchallenge.com

ussales@methapharm.com

ARIDOL® is a registered trademark of Pharmaxis Europe Ltd

Aridol kit carton

PRINCIPAL DISPLAY PANEL

NDC 67850-552-01

Rx Only
Caution: Federal Law Requires Test To Be Administered By a Trained Healthcare Professional Only
Do Not Swallow Aridol Capsules

aridol™
(mannitol inhalation powder)
Bronchial Challenge Test Kit

FOR ORAL INHALATION ONLY

One complete diagnostic kit to measure bronchial hyperresponsiveness

Contents:
3 Blister Cards:
0 mg - 1 capsule
5 mg - 1 capsule
10 mg - 1 capsule
20 mg - 1 capsule
40 mg - 15 capsules
1 Aridol device: For use with enclosed capsules only

See package insert for dosage information.